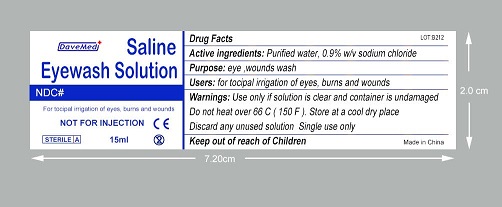 DRUG LABEL: Eye Wash Saline
NDC: 70897-002 | Form: SOLUTION
Manufacturer: Davemed Healthcare Co., Ltd.
Category: otc | Type: HUMAN OTC DRUG LABEL
Date: 20200203

ACTIVE INGREDIENTS: SODIUM CHLORIDE 0.9 mg/100 mL; WATER 99.01 mg/100 mL
INACTIVE INGREDIENTS: SORBIC ACID; BORIC ACID; SODIUM BORATE; HYDROCHLORIC ACID; SODIUM HYDROXIDE; EDETATE DISODIUM

Eye Wash Saline

Purpose

Eye, wounds wash

Active ingredient

Purified water, sodium Chloride

Uses

For tocipal irrigation of eyes, burns and wounds

Warnings

Use only if Solution is clear and container is undamaged

Do not heat over 66°C (150 F). Store at a cool dry place

Discard any unused solution. Single use only

Keep out of reach of children.

If swallowed, get medical help or contact a Poison Control Center right away.

Directions

Not for injection

Inactive ingredients

boric acid, sodium borate, sodium chloride, Hydrochloric acid PRESERVATIVE ADDED: edetate disodium, polyhexamethylene biguanide